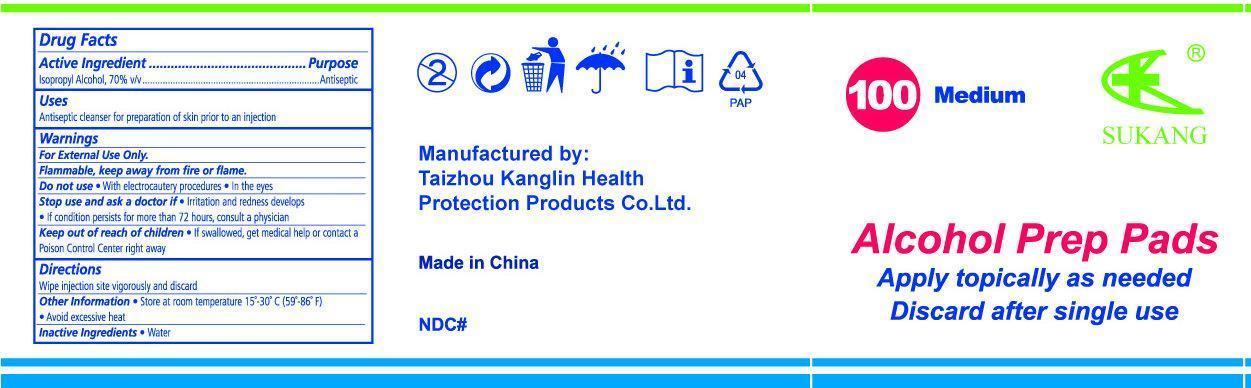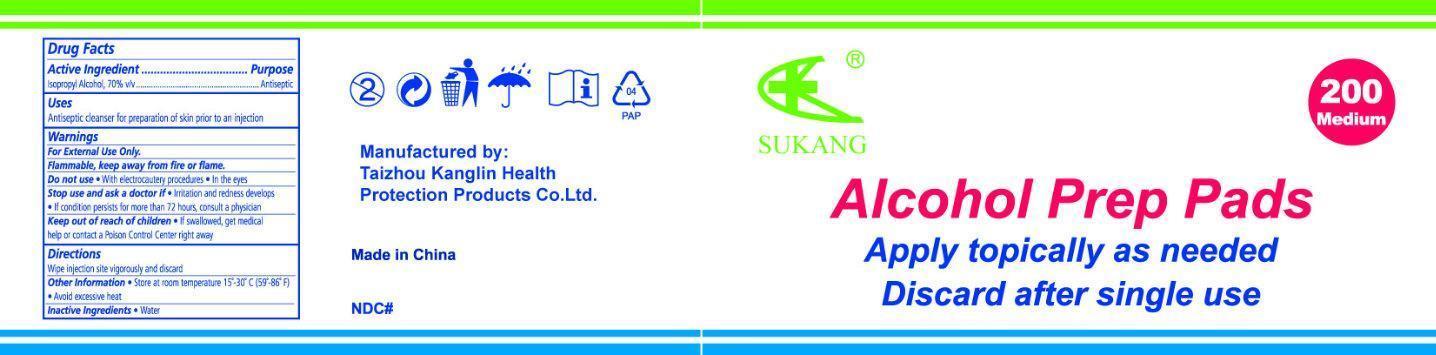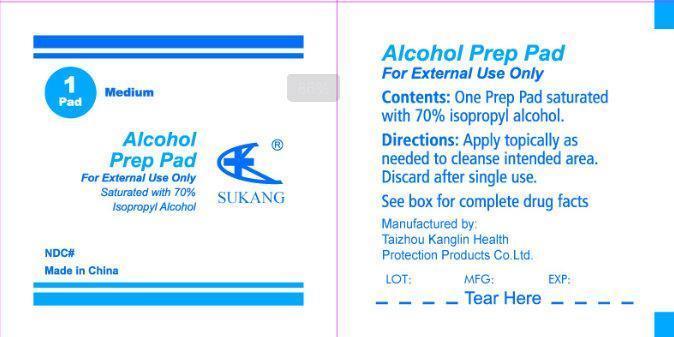 DRUG LABEL: SUKANG Alcohol Prep Pads Medium
NDC: 22408-000 | Form: LIQUID
Manufacturer: Taizhou Kanglin Health Protection Products Co Ltd
Category: otc | Type: HUMAN OTC DRUG LABEL
Date: 20130213

ACTIVE INGREDIENTS: ALCOHOL 70 g/100 g
INACTIVE INGREDIENTS: WATER

SUKANG Alcohol Prep Pads Medium

Active Ingredient

Isopropyl Alcohol, 70% v/v

Purpose

Antiseptic

Uses

Antiseptic cleanser for preparation of skin prior to an injection.

Warnings

For external use only.

Flammable, keep away from fire or flame.

Do not use

- with electrocautery procedures
- in the eyes

Stop use and ask a doctor if

- irritation and redness develops
- if condition persists for more than 72 hours, consult a physician

Keep out of reach of children

- If swallowed, get medical help or contact a Poison Control Center right away.

Directions

Wipe injection site vigorously and discard.

Other Information

- Store at room temperature 15 degrees - 30 degrees C (59 degrees-86 degrees F)
- Avoid excessive heat

Inactive Ingredient

water